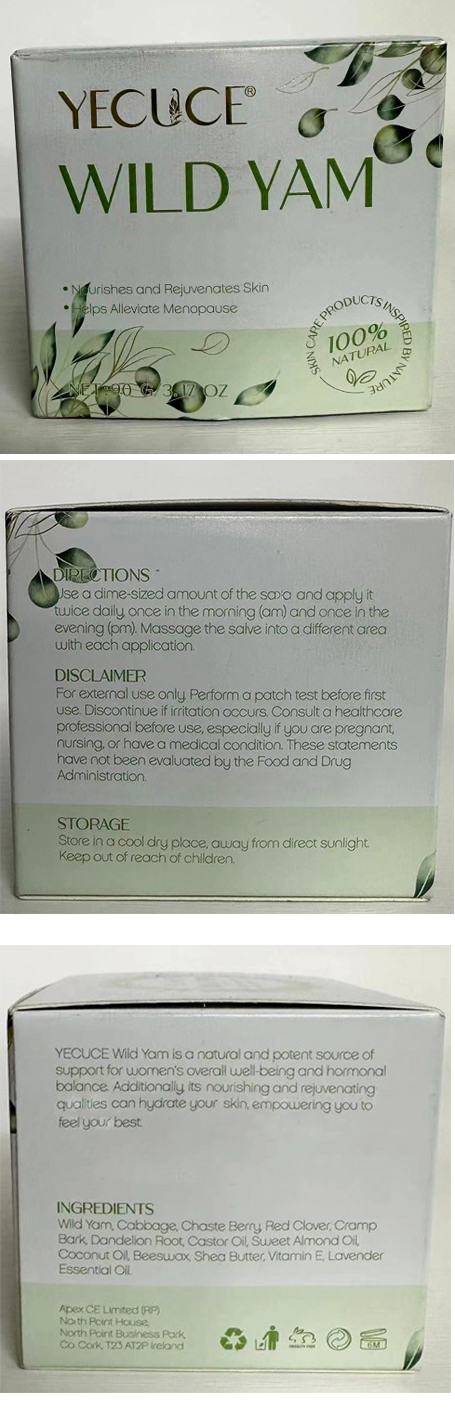 DRUG LABEL: YECUCE Wild Yam Cream
NDC: 83804-004 | Form: CREAM
Manufacturer: Shenzhen Shandian Jingling Technology Co., Ltd.
Category: otc | Type: HUMAN OTC DRUG LABEL
Date: 20250609

ACTIVE INGREDIENTS: DIOSCOREA VILLOSA TUBER 1 g/100 g
INACTIVE INGREDIENTS: FRANKINCENSE; LAVENDER OIL; TRIFOLIUM PRATENSE FLOWER; PEG-8 BEESWAX; VITEX AGNUS-CASTUS WHOLE; THEOBROMA CACAO WHOLE; AVOCADO OIL; OLIVE OIL

83804-004 YECUCE Wild Yam Cream

ACTIVE INGREDIENT

DIOSCOREA VILLOSA TUBER

PURPOSE

Nourishes and Rejuvenates Skin

KEEP OUT OF REACH OF CHILDREN SECTION

INDICATIONS AND USAGE

YECUCE Wild Yam is a natural and potent source ofsupport for women's overall well.being and hormonalbalance Additionally its nounishing and rejuvenatingqualities can hydrate your skin, empowering you tofeel your best

WARNINGS

For external use only

WHEN USING

Perform a patch test before firstuse, Discontinue if irritation occurs, Consuit a heaithcareprofessional before use, especially if you are pregnant,nursing, or have a medical condition, These statementshave not been evaluated by the Food and DrugAdministration

DOSAGE AND ADMINISTRATION

Use a dime sized amount of the soa and apply ittwice daily once in the morning (am) and once in theevening (pm). Massage the save into a different areawith each application.

INACTIVE INGREDIENT

PEG-8 BEESWAX
LAVENDER OIL
FRANKINCENSE
TRIFOLIUM PRATENSE FLOWER
OLIVE OIL
THEOBROMA CACAO WHOLE
AVOCADO OIL
VITEX AGNUS-CASTUS WHOLE